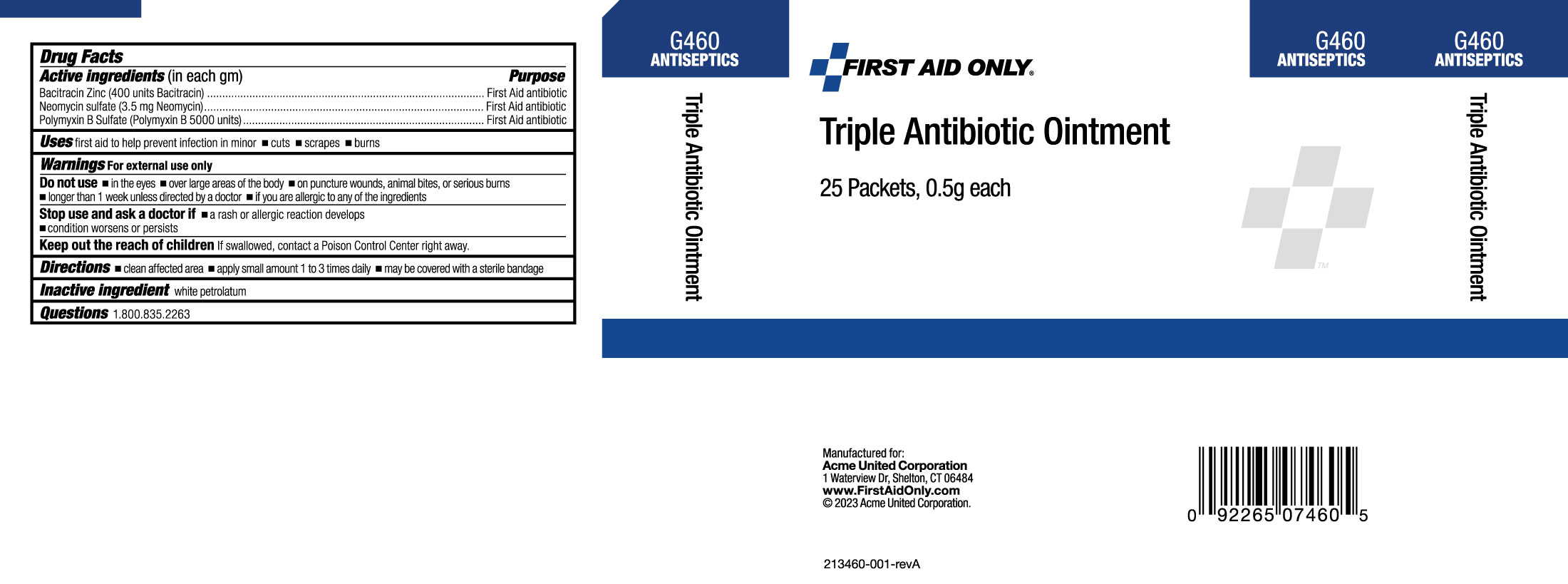 DRUG LABEL: Triple Antibiotic
NDC: 0924-5604 | Form: OINTMENT
Manufacturer: Acme United Corporation
Category: otc | Type: HUMAN OTC DRUG LABEL
Date: 20241119

ACTIVE INGREDIENTS: BACITRACIN ZINC 400 [iU]/1 g; NEOMYCIN SULFATE 3.5 mg/1 g; POLYMYXIN B SULFATE 5000 [iU]/1 g
INACTIVE INGREDIENTS: PETROLATUM

First Aid Only Triple Antibiotic Ointment

Drug Facts

Active Ingredient (in each gram)

Bacitracin Zinc (400 units Bacitracin)

Neomycin Sulfate (3.5 mg Neomycin)

Polymyxin B Sulfate (Polymyxin B 5000 units)

Purpose

First Aid Antibiotic

First Aid Antibiotic

First Aid Antibiotic

Uses

First aid to help prevent infection in minor cuts, scrapes and burns

Warnings

For external use only

Do not use:

- in the eyes
- over large areas of the body
- on puncture wounds, animal bites, or serious burns
- longer than 1 week unless directed by a doctor
- if you are allergic to any of the ingredients

Stop use and ask a doctor if:

- a rash or allergic reaction develops
- condition worsens or persists

Keep out the reach of children.

Directions

- Clean the affected area.
- Apply a small amount of product 1 to 3 times daily
- may be covered with a sterile bandage

Inactive Ingredient

White Petrolatum

Questions

1-800-835-2263

Box Label